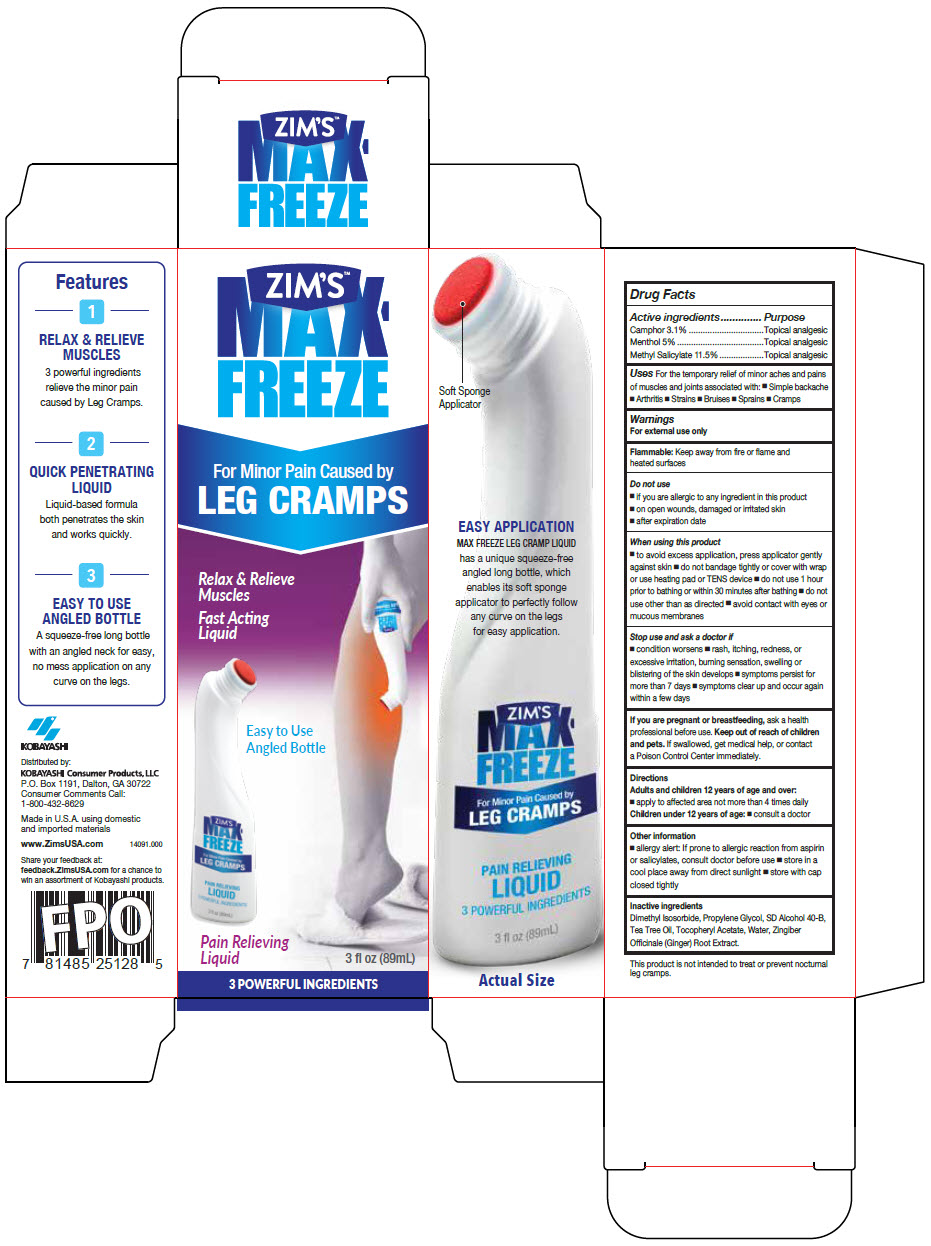 DRUG LABEL: ZIMS MAX FREEZE 
NDC: 54273-011 | Form: LIQUID
Manufacturer: KOBAYASHI Healthcare International, Inc.
Category: otc | Type: HUMAN OTC DRUG LABEL
Date: 20231116

ACTIVE INGREDIENTS: CAMPHOR (SYNTHETIC) 31 mg/1 mL; MENTHOL, UNSPECIFIED FORM 50 mg/1 mL; METHYL SALICYLATE 115 mg/1 mL
INACTIVE INGREDIENTS: DIMETHYL ISOSORBIDE; PROPYLENE GLYCOL; ALCOHOL; TEA TREE OIL; .ALPHA.-TOCOPHEROL ACETATE; WATER; GINGER

ZIM'S™ MAX-FREEZE LEG CRAMP

Drug Facts

ACTIVE INGREDIENT

Active ingredients | Purpose
Camphor 3.1% | Topical analgesic
Menthol 5% | Topical analgesic
Methyl Salicylate 11.5% | Topical analgesic

Uses

For the temporary relief of minor aches and pains of muscles and joints associated with:

- Simple backache
- Arthritis
- Strains
- Bruises
- Sprains
- Cramps

Warnings

For external use only

Flammable

Keep away from fire or flame and heated surfaces

Do not use

- if you are allergic to any ingredient in this product
- on open wounds, damaged or irritated skin
- after expiration date

When using this product

- to avoid excess application, press applicator gently against skin
- do not bandage tightly or cover with wrap or use heating pad or TENS device
- do not use 1 hour prior to bathing or within 30 minutes after bathing
- do not use other than as directed
- avoid contact with eyes or mucous membranes

Stop use and ask a doctor if

- condition worsens
- rash, itching, redness, or excessive irritation, burning sensation, swelling or blistering of the skin develops
- symptoms persist for more than 7 days
- symptoms clear up and occur again within a few days

PREGNANCY OR BREAST FEEDING

If you are pregnant or breastfeeding, ask a health professional before use.

Keep out of reach of children and pets. If swallowed, get medical help, or contact a Poison Control Center immediately.

Directions

Adults and children 12 years of age and over:

- apply to affected area not more than 4 times daily

Children under 12 years of age:

- consult a doctor

Other information

- allergy alert: If prone to allergic reaction from aspirin or salicylates, consult doctor before use
- store in a cool place away from direct sunlight
- store with cap closed tightly

Inactive ingredients

Dimethyl Isosorbide, Propylene Glycol, SD Alcohol 40-B, Tea Tree Oil, Tocopheryl Acetate, Water, Zingiber Officinale (Ginger) Root Extract.

Distributed by:
KOBAYASHI Consumer Products, LLC
P.O. Box 1191, Dalton, GA 30722

PRINCIPAL DISPLAY PANEL - 89 mL Bottle Carton

ZIM'S™
MAX-
FREEZE

For Minor Pain Caused by
LEG CRAMPS

Relax & Relieve
Muscles

Fast Acting
Liquid

Easy to Use
Angled Bottle

Pain Relieving
Liquid
3 fl oz (89mL)

3 POWERFUL INGREDIENTS